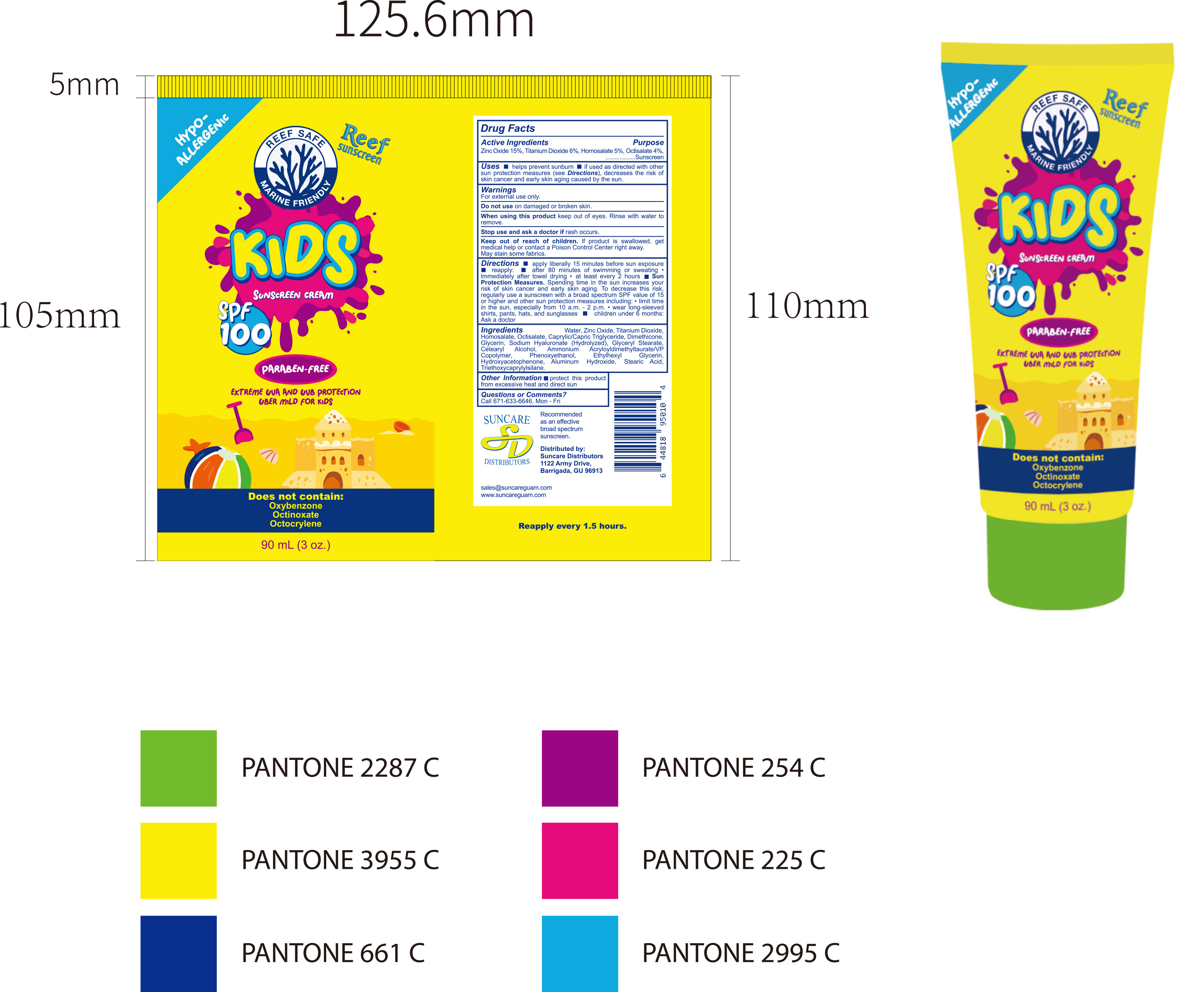 DRUG LABEL: Sunscreen Cream
NDC: 84938-012 | Form: CREAM
Manufacturer: Foshan Sugar Max Cosmetics CO.,Ltd
Category: otc | Type: HUMAN OTC DRUG LABEL
Date: 20251217

ACTIVE INGREDIENTS: HOMOSALATE 0.05 g/1 mL; OCTISALATE 0.04 g/1 mL; ZINC OXIDE 0.15 g/1 mL; TITANIUM DIOXIDE 0.06 g/1 mL
INACTIVE INGREDIENTS: TRIETHOXYCAPRYLYLSILANE; SODIUM HYALURONATE; CETEARYL ALCOHOL; AQUA; STEARIC ACID; ALUMINUM HYDROXIDE; DIMETHICONE; GLYCERIN; AMMONIUM ACRYLOYLDIMETHYLTAURATE/VP COPOLYMER; CAPRYLIC/CAPRIC TRIGLYCERIDE; ETHYLHEXYLGLYCERIN; PHENOXYETHANOL; HYDROXYACETOPHENONE; GLYCERYL STEARATE

84938-012 Sunscreen Cream

ACTIVE INGREDIENT

Zinc Oxide 15%, Titanium Dioxide 6%, Homosalate 5%, Octisalate 4%

PURPOSE

Sunscreen

INDICATIONS AND USAGE

Uses helps prevent sunburn if used as directed with other sun protection measures (see Directions), decreases the risk of skin cancer and early skin aging caused by the sun.

WARNINGS

For external use only.

Do not use on damaged or broken skin.

When using this product keep out of eyes. Rinse with water to remove.

Stop use and ask a doctor if rash occurs

Keep out of reach of children. lf product is swallowed, get medical help or contact a Poison Control Center right away. May stain some fabrics

DOSAGE AND ADMINISTRATION

Directions apply liberally 15 minutes before sun exposure reapply: after 80 minutes of swimming or sweatingImmediately after towel drying "at least every 2 hours SunProtection Measures. Spending time in the sun increases yourrisk of skin cancer and early skin aging. To decrease this risk.regularly use a sunscreen with a broad spectrum SPF value of 15 or higher and other sun protection measures including: " limit time in the sun,especially from 10 a.m.-2 p.m."wear long-sleeved children under 6 months:shirts, pants, hats, and sunglassesAsk a doctor.

INACTIVE INGREDIENT

Aqua (Water)
Caprylic/Capric Triglyceride
Dimethicone
Glycerin
Sodium Hyaluronate (Hydrolyzed)
Glyceryl Stearate
Cetearyl Alcohol
Ammonium Acryloyldimethyltaurate/VP Copolymer
Phenoxyethanol
Ethylhexyl Glycerin
Hydroxyacetophenone
Aluminum Hydroxide
Stearic Acid
Triethoxycaprylylsilane